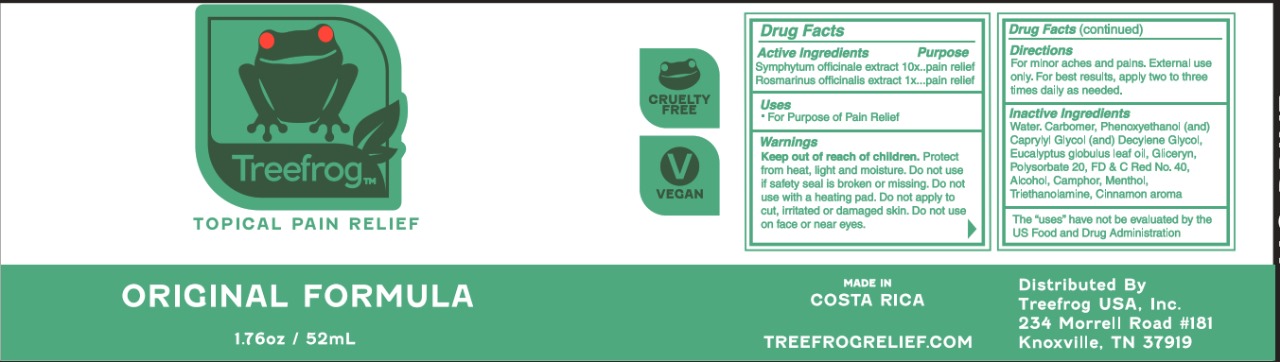 DRUG LABEL: Tree frog
NDC: 55715-007 | Form: GEL
Manufacturer: Laboratorios Zepol S.A.
Category: homeopathic | Type: HUMAN OTC DRUG LABEL
Date: 20240730

ACTIVE INGREDIENTS: COMFREY ROOT 10 [hp_X]/1 mL; ROSEMARY 1 [hp_X]/1 mL
INACTIVE INGREDIENTS: GLYCERIN; FD&C RED NO. 40; WATER; CARBOMER HOMOPOLYMER, UNSPECIFIED TYPE; PHENOXYETHANOL; CAPRYLYL GLYCOL; EUCALYPTUS GLOBULUS LEAF; ALCOHOL; MENTHOL, UNSPECIFIED FORM; TROLAMINE; POLYSORBATE 20; CINNAMON; DECYLENE GLYCOL; CAMPHOR (NATURAL)

Tree frog

ACTIVE INGREDIENT

Symphytum officinale extract 10X,

Rosmarinus officinale extract 1X.

For Purpose of

Pain Relief

Other ingredients:

Water, Carbomer, Phenoxyethanol (and) Caprylyl Glycol (and) Decylene Glycol, Eucalyptus globulus leaf oil, Gliceryn, Polysorbate 20, FD&C Red No. 40, Alcohol, Camphor, Menthol, Triethanolamine, Cinnamon aroma.

Directions:

For minor aches and pains. External use only.

DOSAGE AND ADMINISTRATION

For best results, apply two to three times daily as needed.

WARNINGS SECTION

Keep out of reach of children.

Protect from heat. light and moisture. Do not use if safety seal is broken or missing. Do not use with a heating pad. Do not apply to cut, irritated or damaged skin. Do not use on face or near eyes.

Package Labeling:

Topical Pain Relief

Original Formula

4 oz / 120 mL

Made in Costa Rica

treefrogrelief.com

Distributed By

Treefrog USA, Inc.

234 Morrell Road #181

Knoxville, TN 37919

Package Labeling

Topical Pain Relief

Original Formula

1.76 oz / 52 mL

treefrogrelief.com

Made in Costa Rica

Distributed By Treefrog USA, Inc.

234 Morrell Road #181 Knoxville, TN 37919